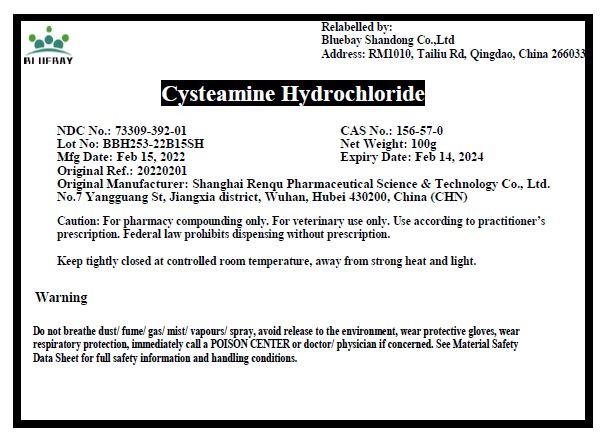 DRUG LABEL: Cysteamine Hydrochloride
NDC: 73309-392 | Form: POWDER
Manufacturer: BLUEBAY SHANDONG CO.,LTD
Category: other | Type: BULK INGREDIENT - ANIMAL DRUG
Date: 20220620

ACTIVE INGREDIENTS: CYSTEAMINE HYDROCHLORIDE 1 g/1 g

Cysteamine Hydrochloride